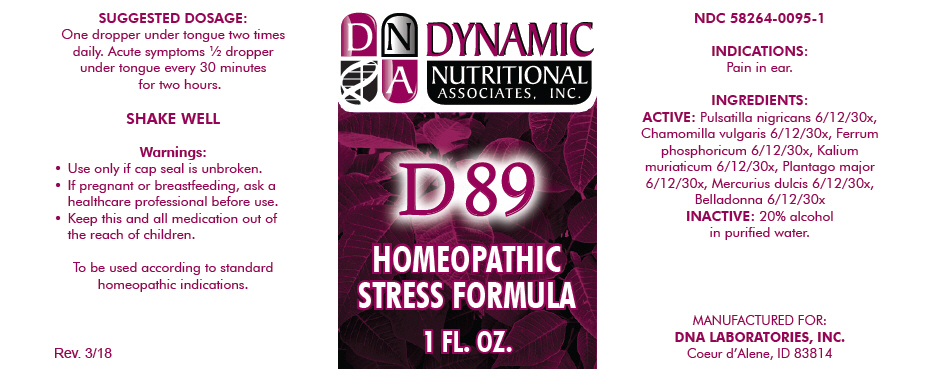 DRUG LABEL: D-89
NDC: 58264-0095 | Form: SOLUTION
Manufacturer: DNA Labs, Inc.
Category: homeopathic | Type: HUMAN OTC DRUG LABEL
Date: 20180703

ACTIVE INGREDIENTS: ANEMONE PRATENSIS 6 [hp_X]/1 mL; MATRICARIA CHAMOMILLA 6 [hp_X]/1 mL; FERROSOFERRIC PHOSPHATE 6 [hp_X]/1 mL; POTASSIUM CHLORIDE 6 [hp_X]/1 mL; Plantago major 6 [hp_X]/1 mL; CALOMEL 6 [hp_X]/1 mL; ATROPA BELLADONNA 6 [hp_X]/1 mL
INACTIVE INGREDIENTS: Alcohol; Water

D-89

NDC 58264-0095-1

INDICATIONS

PURPOSE

Pain in ear.

INGREDIENTS

ACTIVE

Pulsatilla nigricans 6/12/30x, Chamomilla vulgaris 6/12/30x, Ferrum phosphoricum 6/12/30x, Kalium muriaticum 6/12/30x, Plantago major 6/12/30x, Mercurius dulcis 6/12/30x, Belladonna 6/12/30x

INACTIVE

20% alcohol in purified water.

SUGGESTED DOSAGE

One dropper under tongue two times daily. Acute symptoms ½ dropper under tongue every 30 minutes for two hours.

STORAGE AND HANDLING

SHAKE WELL

Warnings

- Use only if cap seal is unbroken.

PREGNANCY OR BREAST FEEDING

- If pregnant or breastfeeding, ask a healthcare professional before use.

KEEP OUT OF REACH OF CHILDREN

- Keep this and all medication out of the reach of children.

To be used according to standard homeopathic indications.

PRINCIPAL DISPLAY PANEL - 1 FL. OZ. Bottle Label

DYNAMIC
NUTRITIONAL
ASSOCIATES, INC.

D 89

HOMEOPATHIC
STRESS FORMULA

1 FL. OZ.